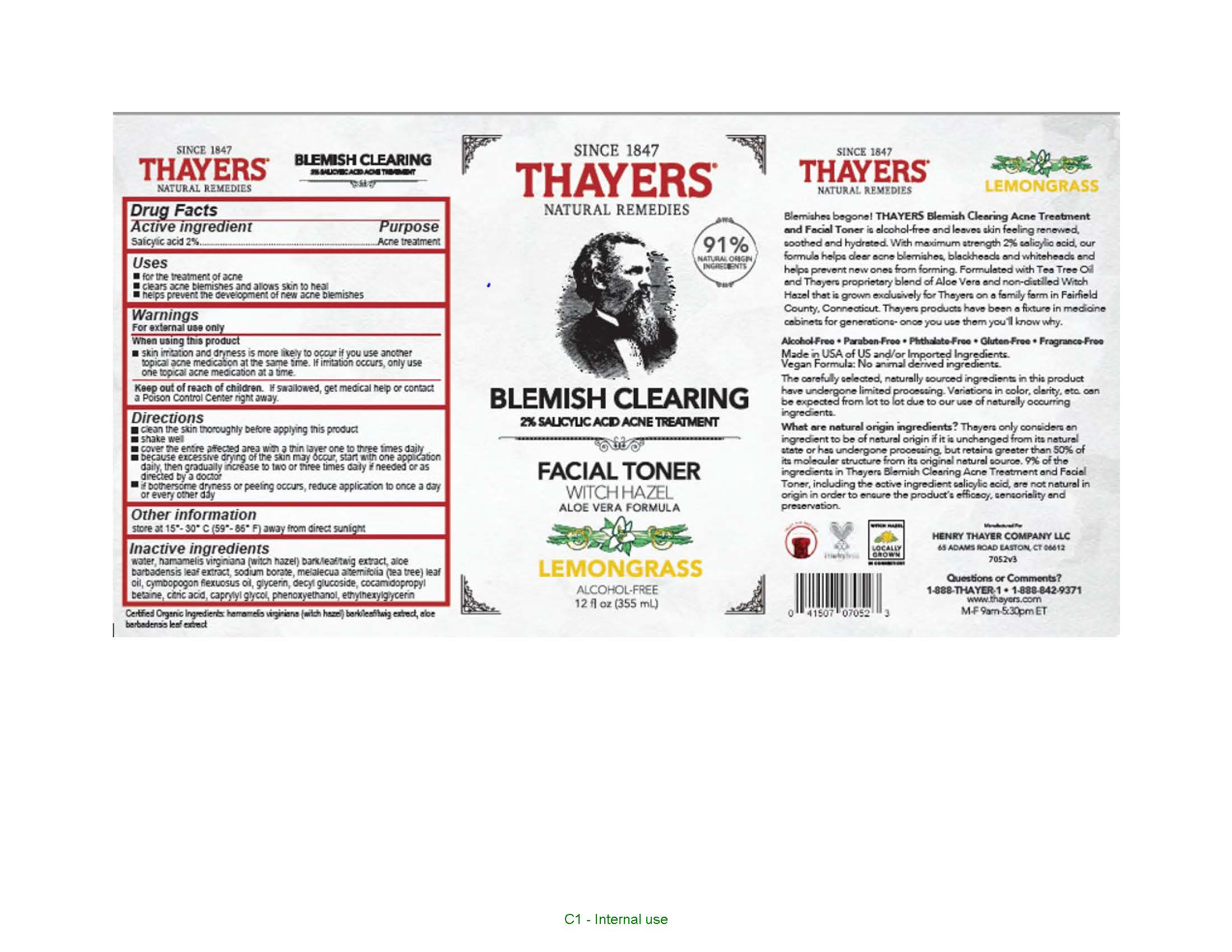 DRUG LABEL: Thayers Since 1847 Natural Remedies Blemish Clearing Witch Hazel Aloe Vera Formula Toner
NDC: 49967-523 | Form: LIQUID
Manufacturer: L'Oreal USA Products Inc
Category: otc | Type: HUMAN OTC DRUG LABEL
Date: 20250324

ACTIVE INGREDIENTS: SALICYLIC ACID 20 mg/1 mL
INACTIVE INGREDIENTS: WATER; HAMAMELIS VIRGINIANA TOP; ALOE VERA LEAF; SODIUM BORATE; MELALEUCA ALTERNIFOLIA LEAF; EAST INDIAN LEMONGRASS OIL; GLYCERIN; DECYL GLUCOSIDE; COCAMIDOPROPYL BETAINE; CITRIC ACID MONOHYDRATE; CAPRYLYL GLYCOL; PHENOXYETHANOL; ETHYLHEXYLGLYCERIN

Drug Facts

Active ingredient

Salicylic acid 2%

Purpose

Acne treatment

Uses

• for the treatment of acne
• clears acne blemishes and allows skin to heal
• helps prevent the development of new acne blemishes

Warnings

For external use only

When using this product

skin irritation and dryness is more likely to occur if you use another topical acne medication at the same time. If irritation occurs, only use one topical acne medication at a time.

Keep out of reach of children.

If swallowed, get medical help or contact a Poison Control Center right away.

Directions

• clean the skin thoroughly before applying this product
• shake well
• cover the entire affected area with a thin layer one to three times daily
• because excessive drying of the skin may occur, start with one application daily, then gradually increase to two or three times daily if needed or as directed by a doctor
• if bothersome dryness or peeling occurs, reduce application to once a day or every other day

Other information

store at 15°-30° C (59°-86° F) away from direct sunlight

Inactive ingredients

water, hamamelis virginiana (witch hazel), bark/leaf/twig extract, aloe barbadensis leaf extract, sodium borate, melalecua alternifolia (tea tree) leaf oil, cymbopogon flexuosus oil, glycerin, decyl glucoside, cocamidopropyl betaine, citric acid, caprylyl glycol, phenoxyethanol, ethylhexylglycerin